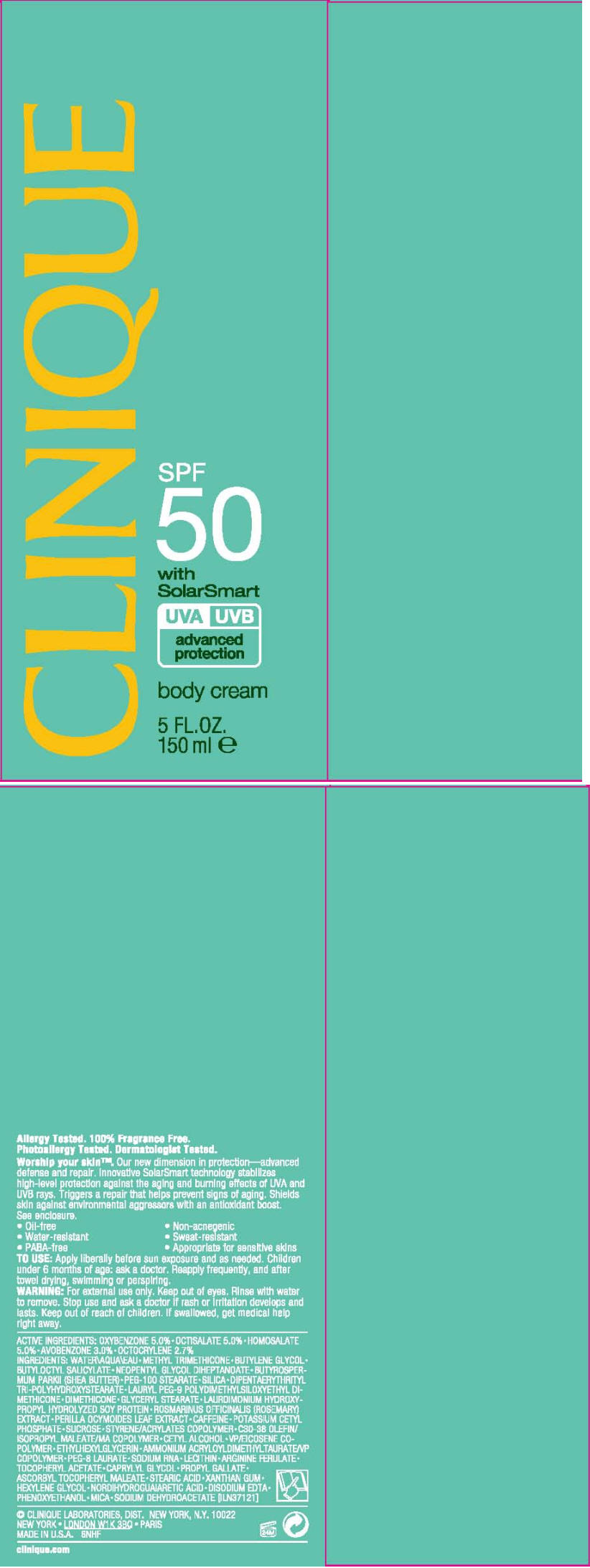 DRUG LABEL: CLINIQUE 
NDC: 49527-734 | Form: CREAM
Manufacturer: CLINIQUE  LABORATORIES INC.
Category: otc | Type: HUMAN OTC DRUG LABEL
Date: 20111014

ACTIVE INGREDIENTS: oxybenzone 5 mL/100 mL; octisalate 5 mL/100 mL; homosalate 5 mL/100 mL; avobenzone 3 mL/100 mL; octocrylene 2.7 mL/100 mL
INACTIVE INGREDIENTS: water; methyl trimethicone; butylene glycol; butyloctyl salicylate; neopentyl glycol diheptanoate; shea butter; peg-100 stearate; silicon dioxide; dimethicone; glyceryl monostearate; rosemary; perilla frutescens leaf; caffeine; potassium cetyl phosphate; sucrose; cetyl alcohol; ethylhexylglycerin; peg-8 laurate; alpha-tocopherol acetate; caprylyl glycol; stearic acid; xanthan gum; maltodextrin; ferulic acid; hexylene glycol; masoprocol; edetate disodium; phenoxyethanol; mica; sodium dehydroacetate

CLINIQUE
SPF
50
with
SolarSmart

TO USE

Apply liberally before sun exposure and as needed. Children under 6 months of age: ask a doctor. Reapply frequently, and after towel drying, swimming or perspiring.

WARNING

For external use only. Keep out of eyes. Rinse with water to remove.

Stop use and ask a doctor if rash or irritation develops and lasts.

Keep out of reach of children. If swallowed, get medical help right away.

ACTIVE INGREDIENTS

OXYBENZONE 5.0% • OCTISALATE 5.0% • HOMOSALATE 5.0% • AVOBENZONE 3.0% • OCTOCRYLENE 2.7%

INGREDIENTS

WATER • METHYL TRIMETHICONE • BUTYLENE GLYCOL • BUTYLOCTYL SALICYLATE • NEOPENTYL GLYCOL DIHEPTANOATE • BUTYROSPERMUM PARKII (SHEA BUTTER) • PEG-100 STEARATE • SILICA • DIPENTAERYTHRITYL TRI-POLYHYDROXYSTEARATE • LAURYL PEG-9 POLYDIMETHYLSILOXYETHYL DIMETHICONE • DIMETHICOME • GLYCERYL STEARATE • LAURDIMONIUM HYDROXYPROPYL HYDROLYZED SOY PROTEIN • ROSMARINUS OFFICINALIS (ROSEMARY) EXTRACT • PERILLA OCYMOIDES LEAF EXTRACT • CAFFEINE • POTASSIUM CETYL PHOSPHATE • SUCROSE • STYRENE/ACRYLATES COPOLYMER • C30-38 OLEFIN/ISOPROPYL MALEATE/MA COPOLYMER • CETYL ALCOHOL • VP/EICOSENE COPOLYMER • ETHYLHEXYLGLYCERIN • AMMONIUM ACRYLOYLDIMETHYLTAURATE/VP COPOLYMER • PEG-8 LAURATE • SODIUM RNA • LECITHIN • ARGINNE FERULATE • TOCOPHERYL ACETATE • CAPRYLYL GLYCOL • PROPYL GALLATE • ASCORBYL TOCOPHERYL MALEATE • STEARIC ACID • XANTHAN GUM • HEXYLENE GLYCOL • NORDIHYDROGUAIARETIC ACID • DISODIUM EDTA • PHENOXYETHANOL • MICA • SODIUM DEHYDROACETATE [ILN37121]

CLINQUE LABORATORIES, DIST. NEW YORK, N.Y. 10022

PRINCIPAL DISPLAY PANEL - 150 ml Carton

CLINIQUE

SPF
50
with
SolarSmart

UVA UVB
advanced
protection

body cream

5 FL. OZ.
150 ml e